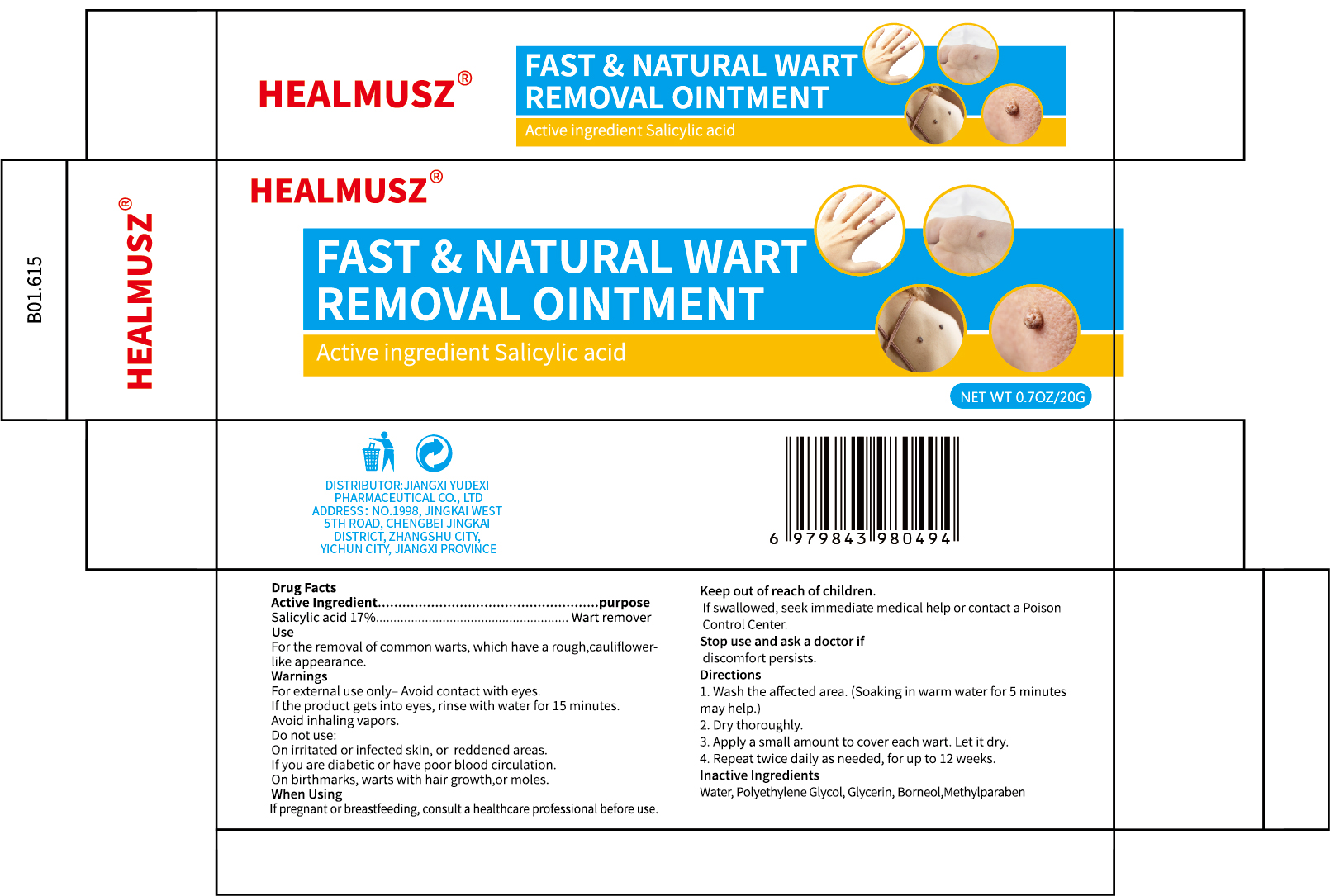 DRUG LABEL: HEALMUSZ FAST NATURAL WART REMOVAL
NDC: 85248-061 | Form: OINTMENT
Manufacturer: Jiangxi Yudexi Pharmaceutical Co., LTD
Category: otc | Type: HUMAN OTC DRUG LABEL
Date: 20260209

ACTIVE INGREDIENTS: SALICYLIC ACID 17 g/100 g
INACTIVE INGREDIENTS: WATER; GLYCERIN; METHYLPARABEN; POLYETHYLENE GLYCOL, UNSPECIFIED; BORNEOL

85248-061

Active Ingredient

Salicylic acid 17%

Purpose

Wart remover

Use

For the removal of common warts, which have a rough,cauliflower-like appearance.

Warnings

For external use only- Avoid contact with eyes. If the product gets into eyes, rinse with water for 15 minutes. Avoid inhaling vapors.

Do not use

On irritated or infected skin, or reddened areas. If you are diabetic or have poor blood circulation. On birthmarks, warts with hair growth,or moles.

When Using

If pregnant or breastfeeding, consult a healthcare professional before use.

Stop Use

Stop use and ask a doctor if discomfort persists.

Ask Doctor

Stop use and ask a doctor if discomfort persists.

Keep Oot Of Reach Of Children

If swallowed, seek immediate medical help or contact a Poison Control Center.

Directions

1.Wash the affected area.(Soaking in warm water for 5 minutes may help.)
2. Dry thoroughly. 3. Apply a small amount to cover each wart. Let it dry 4. Repeat twice daily as needed, for up to 12 weeks.

Inactive ingredients

Water, Polyethylene Glycol, Glycerin, Borneol，Methylparaben.